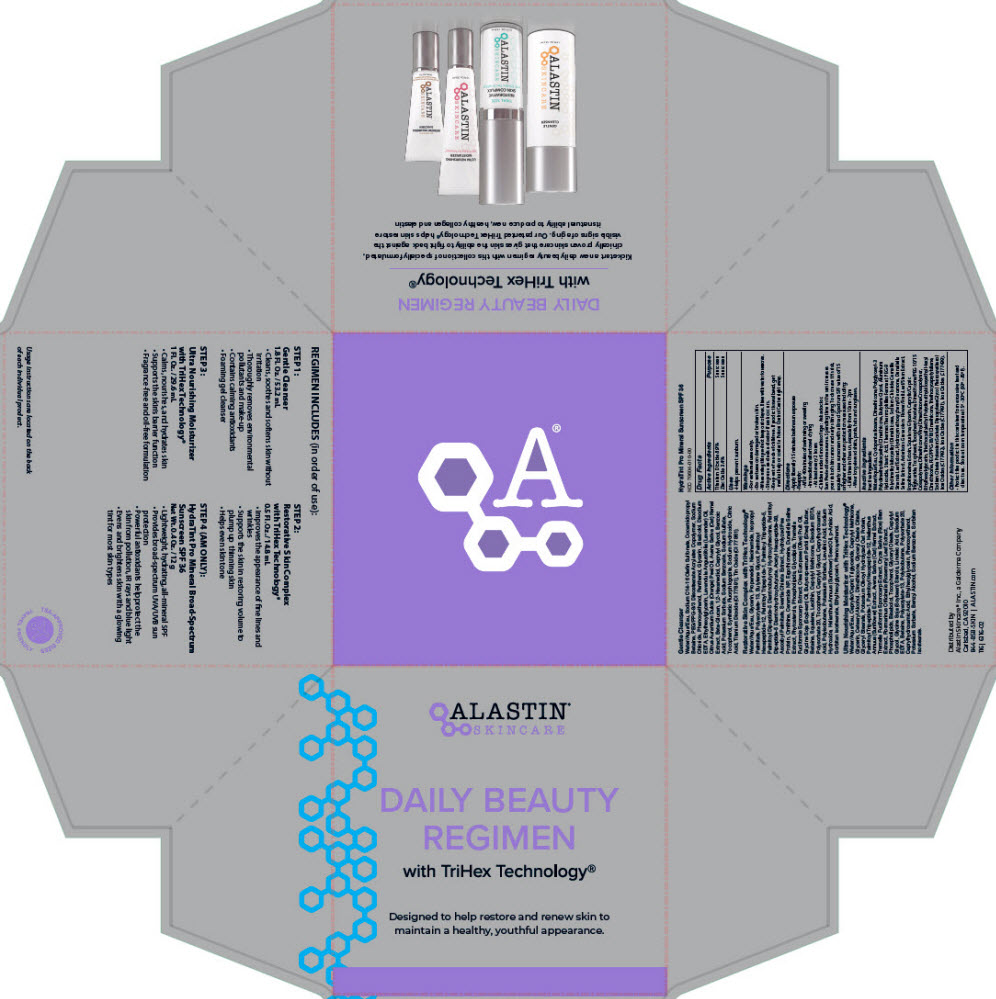 DRUG LABEL: Daily Beauty Regimen with TriHex Technology
NDC: 70604-050 | Form: KIT | Route: TOPICAL
Manufacturer: Alastin Skincare, Inc.
Category: otc | Type: HUMAN OTC DRUG LABEL
Date: 20231220

ACTIVE INGREDIENTS: TITANIUM DIOXIDE 0.089 g/1 g; ZINC OXIDE 0.034 g/1 g
INACTIVE INGREDIENTS: WATER; CYCLOMETHICONE 5; DIMETHICONE; POLYGLYCERYL-3 POLYDIMETHYLSILOXYETHYL DIMETHICONE (4000 MPA.S); BUTYLENE GLYCOL; ALUMINUM HYDROXIDE; STEARIC ACID; THERMUS THERMOPHILUS LYSATE; PEG-9 POLYDIMETHYLSILOXYETHYL DIMETHICONE; SODIUM CHLORIDE; GREEN TEA LEAF; 1-(4-HYDROXY-3-METHOXYPHENYL)-DECAN-3-ONE; DUNALIELLA SALINA; ERGOTHIONEINE; ECTOINE; SQUALANE; GLYCERIN; MEDIUM-CHAIN TRIGLYCERIDES; TOCOPHEROL; .ALPHA.-TOCOPHEROL ACETATE; DIMETHICONE/PEG-10/15 CROSSPOLYMER; DIMETHICONE/VINYL DIMETHICONE CROSSPOLYMER (SOFT PARTICLE); ETHYLHEXYLGLYCERIN; TRIETHOXYSILYLETHYL POLYDIMETHYLSILOXYETHYL HEXYL DIMETHICONE; PEG/PPG-18/18 DIMETHICONE; TRIETHOXYCAPRYLYLSILANE; SODIUM CITRATE, UNSPECIFIED FORM; POTASSIUM SORBATE; DIPROPYLENE GLYCOL; PHENOXYETHANOL; FERRIC OXIDE YELLOW; FERRIC OXIDE RED; FERROSOFERRIC OXIDE

Daily Beauty Regimen with TriHex Technology®

Drug Facts

ACTIVE INGREDIENT

Active Ingredients | Purpose
Titanium Dioxide 8.9% | Sunscreen
Zinc Oxide 3.4% | Sunscreen

Uses

- Helps prevent sunburn.

Warnings

- For external use only.

- Do not use on damaged or broken skin.

- When using this product keep out of eyes. Rinse with water to remove.

- Stop use and ask a doctor if rash occurs.

- Keep out of reach of children. If product is swallowed, get medical help or contact a Poison Control Center right away.

Directions

- Apply liberally 15 minutes before sun exposure
- Reapply:
  - After 40 minutes of swimming or sweating
  - Immediately after towel drying
  - At least every 2 hours
- Children under 6 months of age: Ask a doctor.
  Sun Protection measures. Spending time in the sun increases your risk of skin cancer and early skin aging. To decrease this risk, regularly use a sunscreen with a Broad Spectrum SPF value of 15 or higher and other sun protection measures including:
  - Limit time in the sun, especially from 10am - 2pm
  - Wear long-sleeved shirts, pants, hats and sunglasses.

Inactive Ingredients

Water/Aqua/Eau, Cyclopentasiloxane, Dimethicone, Polyglyceryl-3 Polydimethylsiloxyethyl Dimethicone, Butylene Glycol, Aluminum Hydroxide, Stearic Acid, Thermus Thermophillus Ferment, PEG-9 Polydimethylsiloxyethyl Dimethicone, Sodium Chloride, Camellia Sinensis Leaf Extract, Hydroxymethoxyphenyl Decanone, Dunaliella Salina Extract, Asteriscus Graveolens Flower/Fruit/Leaf/Stem Extract, Ergothioneine, Ectoin, Squalane, Glycerin, Caprylic/Capric Triglyceride, Tocopherol, Tocopheryl Acetate, Dimethicone/PEG-10/15 Crosspolymer, Dimethicone/Vinyl Dimethicone Crosspolymer, Ethylhexylglycerin, Triethoxysilylethyl Polydimethylsiloxyethyl Hexyl Dimethicone, PEG/PPG-18/18 Dimethicone, Triethoxycaprylylsilane, Sodium Citrate, Potassium Sorbate, Dipropylene Glycol, Phenoxyethanol, Iron Oxides (CI 77492), Iron Oxides (CI 77491), Iron Oxides (CI 77499).

Other Information

- Protect the product in this container from excessive heat and direct sun. Store at room temperature 15° - 30°C (59° - 86°F).

Distributed by
Alastin Skincare® Inc., a Galderma Company
Carlsbad, CA 92010

PRINCIPAL DISPLAY PANEL - Kit Carton

ALASTIN®
SKINCARE

DAILY BEAUTY
REGIMEN

with TriHex Technology®

Designed to help restore and renew skin to
maintain a healthy, youthful appearance.